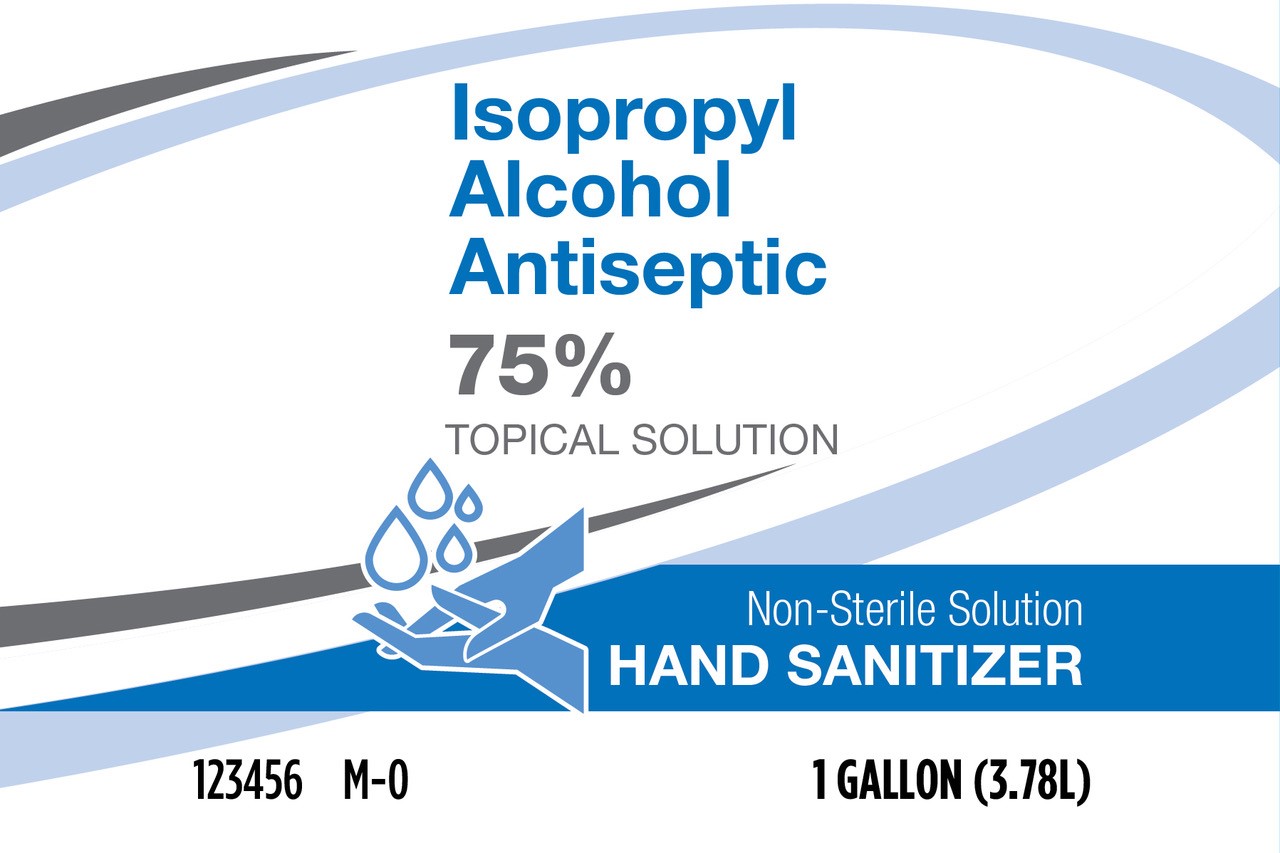 DRUG LABEL: Hand Sanitizer
NDC: 73998-001 | Form: LIQUID
Manufacturer: True Value Company, L.L.C.
Category: otc | Type: HUMAN OTC DRUG LABEL
Date: 20210715

ACTIVE INGREDIENTS: ISOPROPYL ALCOHOL 0.75 mL/1 mL
INACTIVE INGREDIENTS: HYDROGEN PEROXIDE; WATER; GLYCERIN

Hand Sanitizer

DOSAGE AND ADMINISTRATION

Hand sanitizer to help reduce bacteria that potentially can cause disease. For use when soap and water are not available.

Directions: Place enough product on hands to cover all surfaces. Rub hands together until dry.
Supervise children under 6 years of age when using this product to avoid swallowing.

WARNINGS

Warnings. For external use only. Flammable. Keep away from heat or flame. Do not use • in children less than 2 months of age • on open skin wounds When using this product keep out of eyes, ears, and mouth. In case of contact with eyes, rinse eyes thoroughly with water. Stop use and ask a doctor if irritation or rash occurs. These may be signs of a serious condition. Keep out of reach of children. If swallowed, get medical help or contact a Poison Control Center right away.

Inactive ingredients: glycerin, hydrogen peroxide, purified water USP

INDICATIONS AND USAGE

Use[s]: Hand sanitizer to help reduce bacteria that potentially can cause disease. For use when soap and water are not available.

Active ingredient[s] : Isopropyl alcohol 75% v/v

Keep out of reach of children. If swallowed, get medical help or contact a Poison Control Center right away.

Purpose: Antiseptic

PACKAGE LABEL

tion Antiseptic Hand Rub Non-sterile Solution